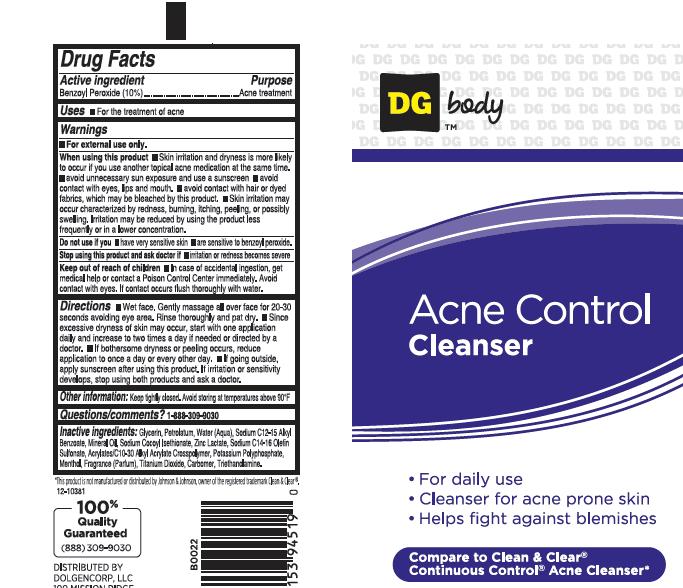 DRUG LABEL: ACNE CONTROL CLEANSER
NDC: 55910-825 | Form: CREAM
Manufacturer: DOLGENCORP INC
Category: otc | Type: HUMAN OTC DRUG LABEL
Date: 20111025

ACTIVE INGREDIENTS: BENZOYL PEROXIDE 10 g/100 g
INACTIVE INGREDIENTS: GLYCERIN; PETROLATUM; WATER; ALKYL (C12-15) BENZOATE ; MINERAL OIL; SODIUM COCOYL ISETHIONATE; ZINC LACTATE; SODIUM C14-16 OLEFIN SULFONATE; POTASSIUM METAPHOSPHATE; MENTHOL; TITANIUM DIOXIDE; CARBOMER 934; TROLAMINE; CARBOMER INTERPOLYMER TYPE A (55000 MPA.S)

DRUG FACTS

ACTIVE INGREDIENT

BENZOYL PEROXIDE 10%

PURPOSE

ACNE TREATMENT

USES

FOR THE TREATMENT OF ACNE.

WARNINGS

FOR EXTERNAL USE ONLY.

WHEN USING THE PRODUCT

- SKIN IRRITATION AND DRYNESS IS MORE LIKELY TO OCCUR IF YOU USE ANOTHER TOPICAL ACNE MEDICATION AT THE SAME TIME.
- AVOID UNNECESSARY SUN EXPOSURE AND USE A SUNSCREEN
- AVOID CONTACT WITH EYES, LIPS AND MOUTH.
- AVOID CONTACT WITH HAIR OR DYED FABRICS, WHICH MAY BE BLEACHED BY THIS PRODUCT.
- SKIN IRRITATION MAY OCCUR CHARACTERIZED BY REDNESS, BURNING, ITCHING, PEELING, OR POSSIBLY SWELLING. IRRITATION MAY BE REDUCED BY USING THE PRODUCT LESS FREQUENTLY OR IN A LOWER CONCENTRATION.

STOP USING THIS PRODUCT AND ASK DOCTOR IF

IRRITATION OR REDNESS BECOMES SEVERE.

KEEP OUT OF REACH OF CHILDREN

IN CASE OF ACCIDENTAL INGESTION, GET MEDICAL HELP OR CONTACT A POISON CONTROL CENTER IMMEDIATELY. AVOID CONTACT WITH EYES. IF CONTACT OCCURS FLUSH THOROUGHLY WITH WATER.

DIRECTIONS

- WET FACE. GENTLY MASSAGE ALL OVER FACE FOR 20-30 SECONDS AVOIDING EYE AREA. RINSE THOROUGHLY AND PAT DRY.
- SINCE EXCESSIVE DRYNES OF SKIN MAY OCCUR, START WITH ONE APPLICATION DAILY AND INCREASE TO TWO TIMES A DAY IF NEEDED OR DIRECTED BY A DOCTOR.
- IF BOTHERSOME DRYNESS OR PEELING OCCURS, REDUCE APPLICATION TO ONCE A DAY OR EVERY OTHER DAY.
- IF GOING OUTSIDE, APPLY SUNSCREEN AFTER USING THIS PRODUCT. IF IRRITATION OR SENSITIVITY DEVELOPS, STOP USING BOTH PRODUCTS AND ASK A DOCTOR.

OTHER INFORMATION

KEEP TIGHTLY CLOSED. AVOID STORING AT TEMPERATURES ABOVE 90 DEGREES FAHRENHEIT.

QUESTIONS OR COMMENTS

1-888-309-9030

INACTIVE INGREDIENTS

GLYCERIN, PETROLATUM, WATER, SODIUM C12-15 ALKYL BENZOATE, MINERAL OIL, SODIUM COCOYL ISETHIONATE, ZINC LACTATE, SODIUM C14-16 OLEFIN SULFONATE, ACRYLATES/C10-30 ALKYL ACRYLATE CROSSPOLYMER, POTASSIUM POLYPHOSPHATE, MENTHOL, FRAGRANCE, TITANIUM DIOXIDE, CARBOMER, TRIETHANOLAMINE.